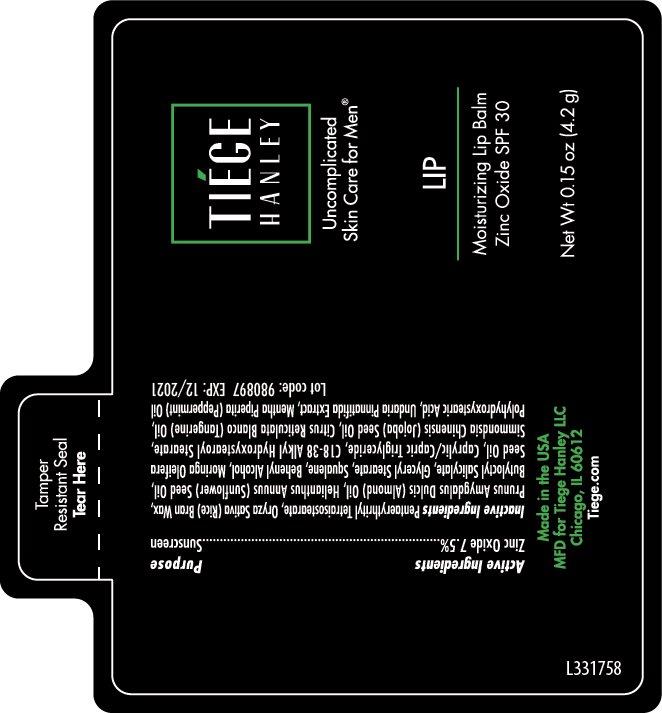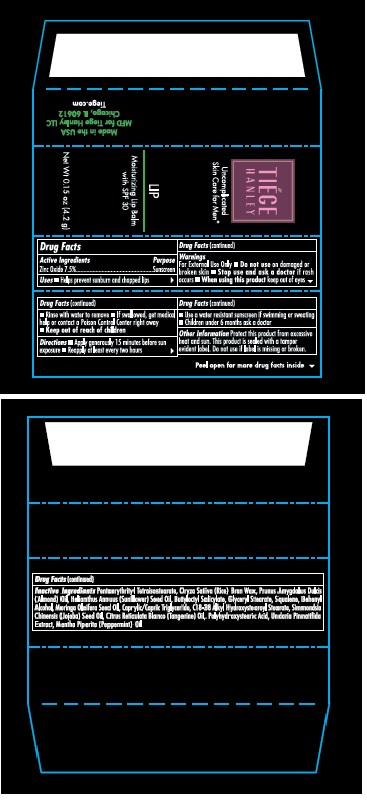 DRUG LABEL: Tiege Hanley Moisturizing Lip Balm SPF 30
NDC: 65692-1004 | Form: STICK
Manufacturer: Raining Rose, Inc.
Category: otc | Type: HUMAN OTC DRUG LABEL
Date: 20200413

ACTIVE INGREDIENTS: ZINC OXIDE 75 mg/1 g
INACTIVE INGREDIENTS: PENTAERYTHRITYL TETRAISOSTEARATE; RICE BRAN; ALMOND OIL; SUNFLOWER OIL; BUTYLOCTYL SALICYLATE; GLYCERYL MONOSTEARATE; SQUALENE; DOCOSANOL; MORINGA OLEIFERA SEED OIL; MEDIUM-CHAIN TRIGLYCERIDES; SYNTHETIC WAX (1200 MW); JOJOBA OIL; MANDARIN OIL; POLYHYDROXYSTEARIC ACID (2300 MW); UNDARIA PINNATIFIDA; PEPPERMINT OIL

Tiege Hanley Moisturizing Lip Balm SPF 30

Drug Facts

Active Ingredients
Zinc Oxide 7.5%

Purpose

Sunscreen

INDICATIONS AND USAGE

Uses • Helps prevent sunburn and chapped lips

Warnings
For External Use Only • Do not use on damaged
or broken skin • Stop use and ask a doctor if rash
occurs • When using this product keep out of eyes.
• Rinse with water to remove • If swallowed get medical
help or contact Poison Control Center right away.
• Keep out of reach of children.

DOSAGE AND ADMINISTRATION

Directions •Apply generously 15 minutes before sun exposure
• Reapply at least every two hours
• Use a water resistant sunscreen if swimming or sweating
• Children under 6 months ask a doctor

Other Information: Protect this product from excessive
heat and sun. This product is sealed with a tamper
evident label. Do not use if label is missing or broken.

INACTIVE INGREDIENT

Inactive Ingredients Pentaerythrityl Tetraisostearate, Oryza Sativa (Rice) Bran Wax, Prunus Amygdalus Dulcis
(Almond) Oil, Helianthus Annuus (Sunflower) Seed Oil, Butyloctyl Salicylate, Glyceryl Stearate, Squalene, Behenyl
Alcohol, Moringa Oleifera Seed Oil, Caprylic/Capric Triglyceride, C18-38 Alkyl Hydroxystearoyl Stearate, Simmondsia
Chinensis (Jojoba) Seed Oil, Citrus Reticulata Blanco (Tangerine) Oil, Polyhydroxystearic Acid, Undaria Pinnatifida
Extract, Mentha Piperita (Peppermint) Oil

Package Labeling

TIEGE

HANLEY

Uncomplicated

Skin Care for Men®

LIP

Moisturizing Lip Balm

with SPF 30

Net Wt 0.15 oz (4.2 g)

Made in the USA

MFD for Tiege Hanley LLC

Chuicago, IL 60612

Tiege.com

Tube Label

Box Label

res